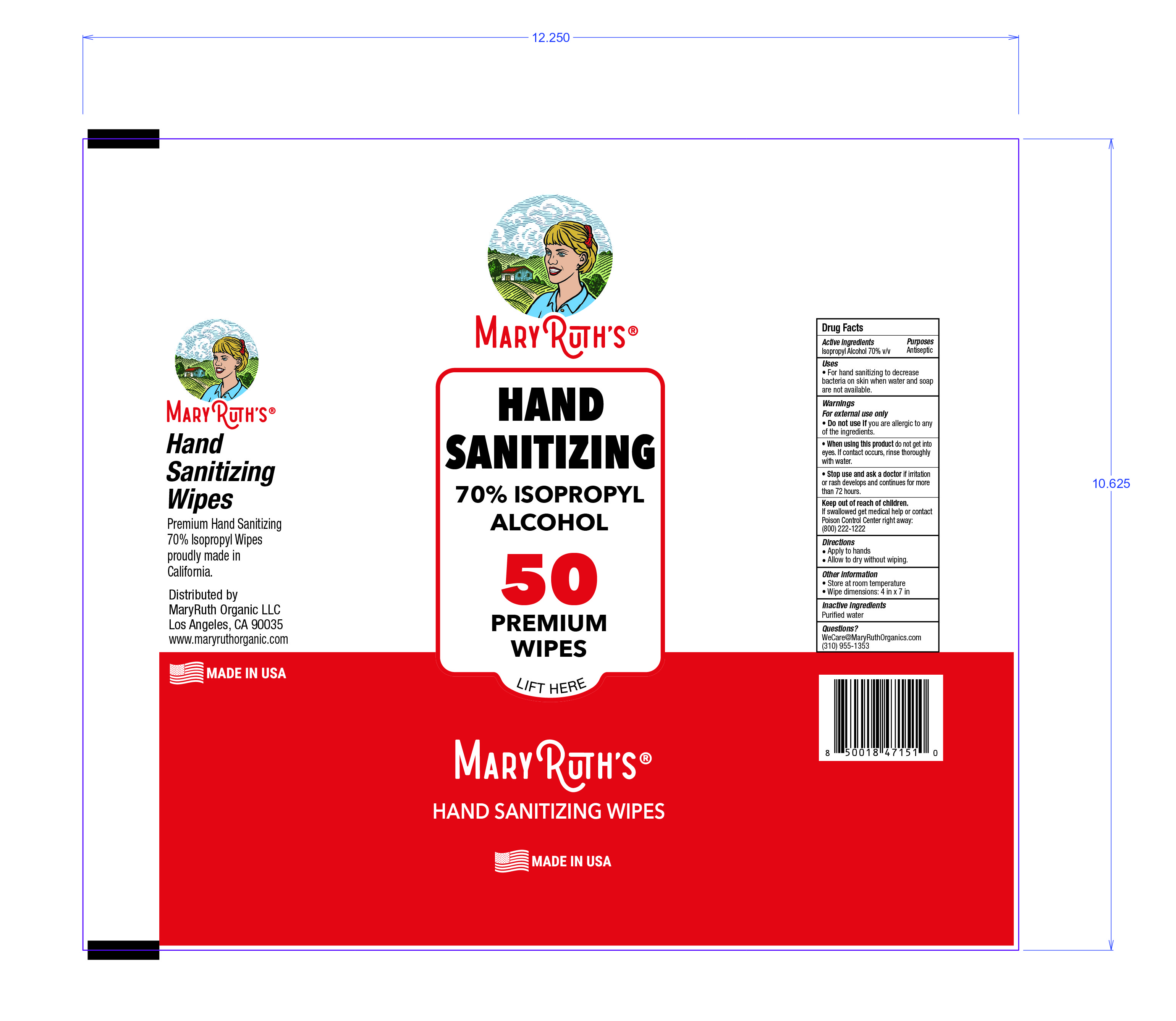 DRUG LABEL: MaryRuth Organics Hand Sanitizing Wipes
NDC: 77890-003 | Form: CLOTH
Manufacturer: Angel Tree Products Inc.
Category: otc | Type: HUMAN OTC DRUG LABEL
Date: 20201007

ACTIVE INGREDIENTS: ISOPROPYL ALCOHOL 70 1/100 1
INACTIVE INGREDIENTS: WATER 30 1/100 1

Active Ingredient(s)

Isopropyl Alcohol 70% v/v. Purpose: Antiseptic

Purpose

Antiseptic

Use

For hand sanitizing to decrease bacteria on skin when soap and water are not available.

Warnings

For external use only. Flammable. Keep away from heat or flame

Do not use

if you are allergic to any of the ingredients

When using this product keep out of eyes, ears, and mouth. In case of contact with eyes, rinse eyes thoroughly with water.
Keep out of reach of children. If swallowed, get medical help or contact a Poison Control Center right away.

Stop use and ask a doctor if irritation or rash occurs and continues for more than 72 hours. These may be signs of a serious condition.

Keep out of reach of children. If swallowed, get medical help or contact a Poison Control Center right away.

Directions

Apply to hands - Allow to dry without wiping.

Other information

- Store at room temperature - Wipe dimensions: 4 in x 7 in

Inactive ingredients

purified water USP

Package Label - Principal Display Panel

50 Wipes NDC: 77890-003-03